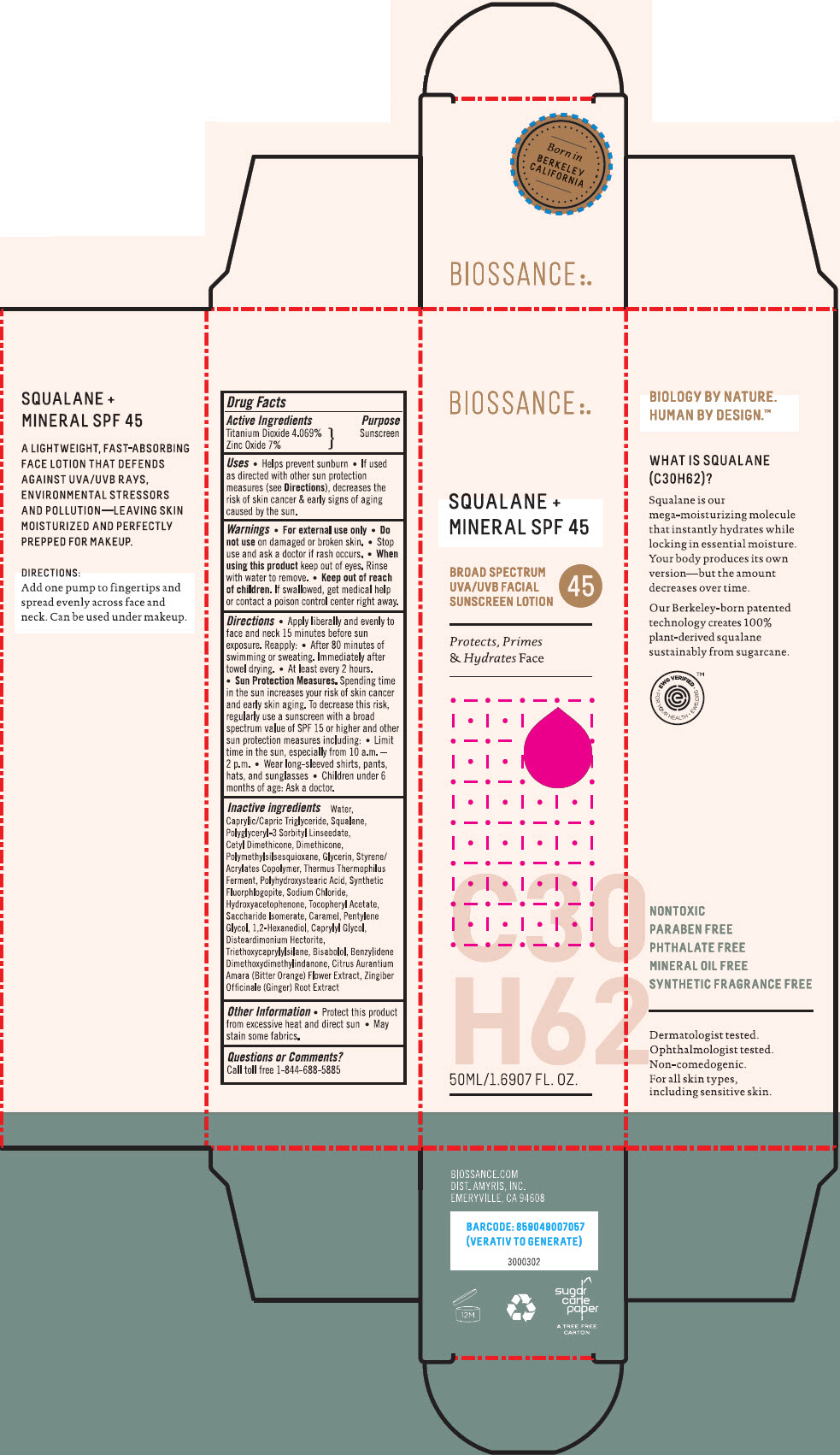 DRUG LABEL: Squalane plus Mineral SPF 45
NDC: 73517-123 | Form: CREAM
Manufacturer: Amyris, Inc.
Category: otc | Type: HUMAN OTC DRUG LABEL
Date: 20200225

ACTIVE INGREDIENTS: Titanium Dioxide 40.69 mg/1 mL; Zinc Oxide 70 mg/1 mL
INACTIVE INGREDIENTS: Water; Medium-Chain Triglycerides; Squalane; Dimethicone; Polymethylsilsesquioxane (4.5 Microns); Glycerin; STYRENE/ACRYLAMIDE COPOLYMER (500000 MW); Thermus Thermophilus Lysate; POLYHYDROXYSTEARIC ACID (2300 MW); Sodium Chloride; Hydroxyacetophenone; .Alpha.-Tocopherol Acetate; Saccharide Isomerate; Caramel; Pentylene Glycol; 1,2-Hexanediol; Caprylyl Glycol; Disteardimonium Hectorite; Triethoxycaprylylsilane; Levomenol; Benzylidene Dimethoxydimethylindanone; Citrus Aurantium Flower; Ginger

Squalane plus Mineral SPF 45

Drug Facts

Active Ingredients

Titanium Dioxide 4.069%
Zinc Oxide 7%

Purpose

Sunscreen

Uses

- Helps prevent sunburn
- If used as directed with other sun protection measures (see Directions), decreases the risk of skin cancer & early signs of aging caused by the sun.

Warnings

- For external use only

- Do not use on damaged or broken skin.

- Stop use and ask a doctor if rash occurs.

- When using this product keep out of eyes. Rinse with water to remove.

- Keep out of reach of children. If swallowed, get medical help or contact a poison control center right away.

Directions

- Apply liberally and evenly to face and neck 15 minutes before sun exposure. Reapply:
  - After 80 minutes of swimming or sweating. Immediately after towel drying.
  - At least every 2 hours.
- Sun Protection Measures. Spending time in the sun increases your risk of skin cancer and early skin aging. To decrease this risk, regularly use a sunscreen with a broad spectrum value of SPF 15 or higher and other sun protection measures including:
  - Limit time in the sun, especially from 10 a.m. – 2 p.m.
  - Wear long-sleeved shirts, pants, hats, and sunglasses
- Children under 6 months of age: Ask a doctor.

Inactive ingredients

Water, Caprylic/Capric Triglyceride, Squalane, Polyglyceryl-3 Sorbityl Linseedate, Cetyl Dimethicone, Dimethicone, Polymethylsilsesquioxane, Glycerin, Styrene/Acrylates Copolymer, Thermus Thermophilus Ferment, Polyhydroxystearic Acid, Synthetic Fluorphlogopite, Sodium Chloride, Hydroxyacetophenone, Tocopheryl Acetate, Saccharide Isomerate, Caramel, Pentylene Glycol, 1,2-Hexanediol, Caprylyl Glycol, Disteardimonium Hectorite, Triethoxycaprylylsilane, Bisabolol, Benzylidene Dimethoxydimethylindanone, Citrus Aurantium Amara (Bitter Orange) Flower Extract, Zingiber Officinale (Ginger) Root Extract

Other Information

- Protect this product from excessive heat and direct sun
- May stain some fabrics.

Questions or Comments?

Call toll free 1-844-688-5885

PRINCIPAL DISPLAY PANEL - 50 ML Tube Carton

BIOSSANCE

SQUALANE +
MINERAL SPF 45

BROAD SPECTRUM
UVA/UVB FACIAL
SUNSCREEN LOTION

45

Protects, Primes
& Hydrates Face

50ML/1.6907 FL. OZ.